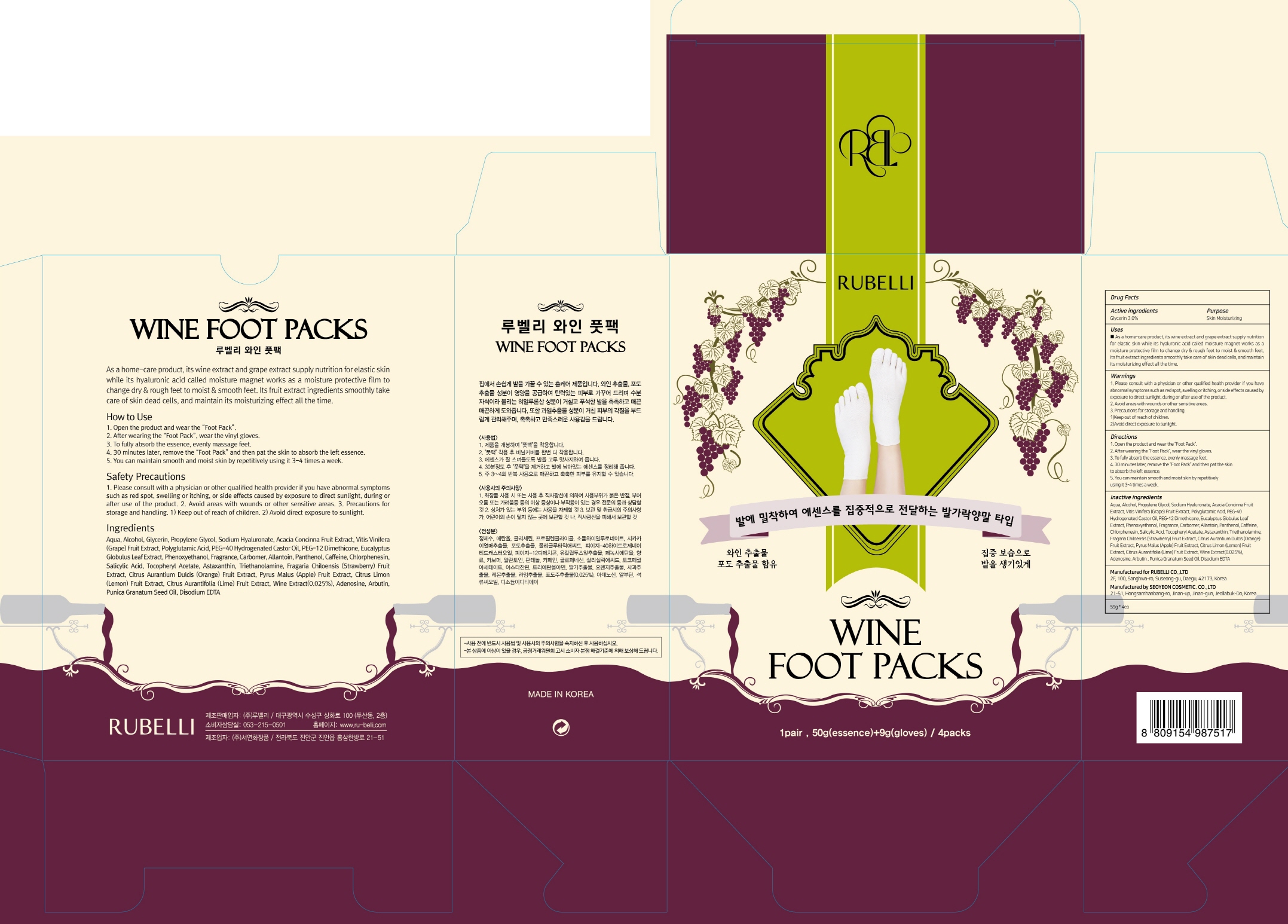 DRUG LABEL: Rubelli Wine Foot Packs
NDC: 71006-030 | Form: PATCH
Manufacturer: RUBELLI CO.,LTD
Category: otc | Type: HUMAN OTC DRUG LABEL
Date: 20170925

ACTIVE INGREDIENTS: Glycerin 1.50 g/50 g
INACTIVE INGREDIENTS: WATER; Alcohol

ACTIVE INGREDIENT

Active Ingredient: Glycerin 3.0%

INACTIVE INGREDIENT

Inactive Ingredients: Aqua, Alcohol, Propylene Glycol, Sodium Hyaluronate, Acacia Concinna Fruit Extract, Vitis Vinifera (Grape) Fruit Extract, Polyglutamic Acid, PEG-40 Hydrogenated Castor Oil, PEG-12 Dimethicone, Eucalyptus Globulus Leaf Extract, Phenoxyethanol, Fragrance, Carbomer, Allantoin, Panthenol, Caffeine, Chlorphenesin, Salicylic Acid, Tocopheryl Acetate, Astaxanthin, Triethanolamine, Fragaria Chiloensis (Strawberry) Fruit Extract, Citrus Aurantium Dulcis (Orange) Fruit Extract, Pyrus Malus (Apple) Fruit Extract, Citrus Limon (Lemon) Fruit Extract, Citrus Aurantifolia (Lime) Fruit Extract, Wine Extract(0.025%), Adenosine, Arbutin , Punica Granatum Seed Oil, Disodium EDTA

PURPOSE

Purpose: Skin Moisturizing

WARNINGS

1. Please consult with a physician or other qualified health provider if you have abnormal symptoms such as red spot, swelling or itching, or side effects caused by exposure to direct sunlight, during or after use of the product,. 2. Avoid areas with wounds or other sensitive areas. 3. Precautions for storage and handling. 1)Keep out of reach of children. 2)Avoid direct exposure to sunlight.

KEEP OUT OF REACH OF CHILDREN

Use

As a home-care product, its wine extract and grape extract supply nutrition for elastic skin while its hyaluronic acid called moisture magnet works as a moisture protective film to change dry & rough feet to moist & smooth feet. Its fruit extract ingredients smoothly take care of skin dead cells, and maintain its moisturizing effect all the time.

Directions

1. Open the product and wear the “Foot Pack”. 2. After wearing the “Foot Pack”, wear the vinyl gloves. 3. To fully absorb the essence, evenly massage feet. 4. 30 minutes later, remove the “Foot Pack” and then pat the skin to absorb the left essence. 5. You can maintain smooth and moist skin by repetitively using it 3-4 times a week.